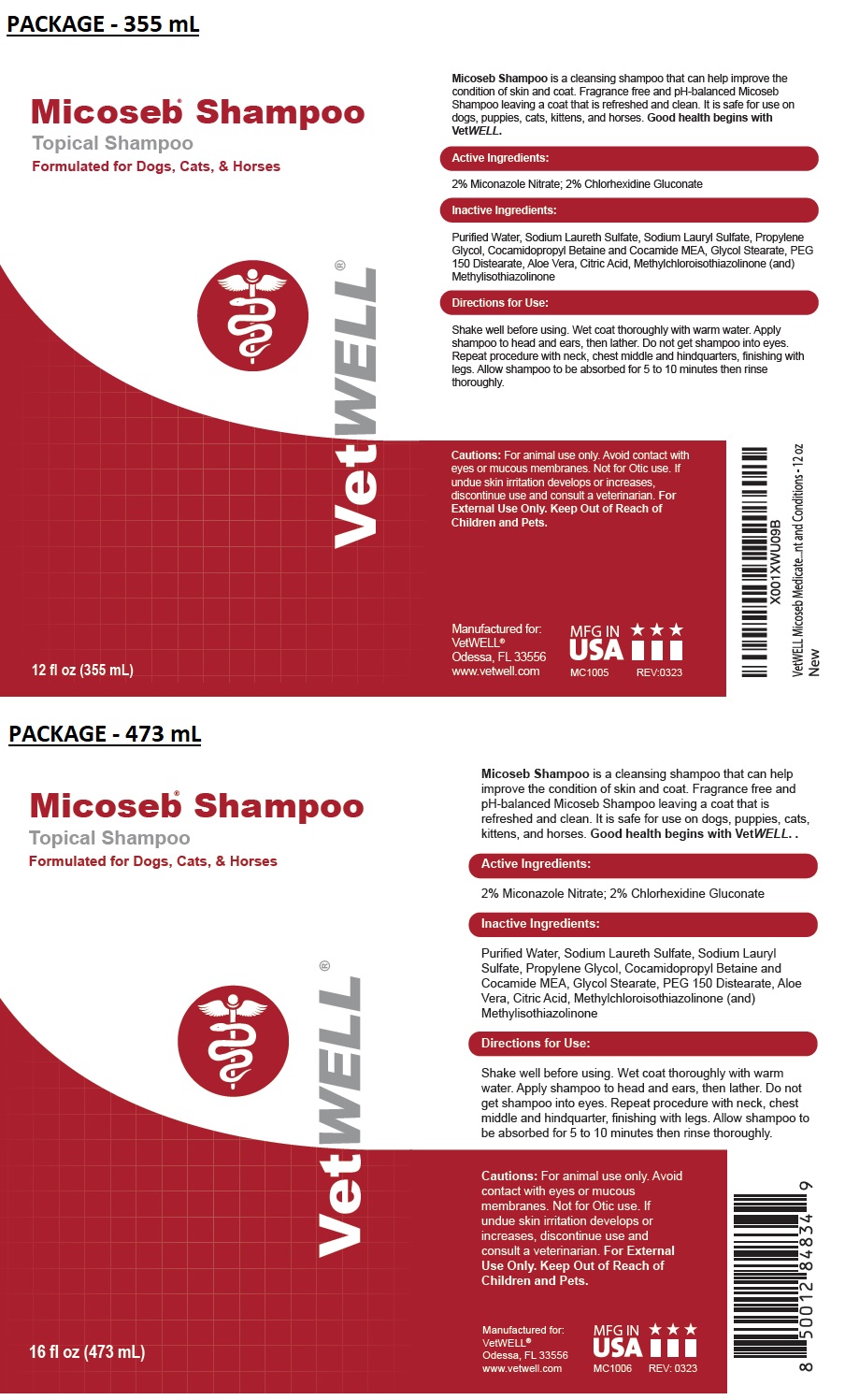 DRUG LABEL: VetWELL Micoseb
NDC: 86090-015 | Form: SHAMPOO
Manufacturer: Pet MD Brands, LLC
Category: animal | Type: OTC ANIMAL DRUG LABEL
Date: 20230908

ACTIVE INGREDIENTS: MICONAZOLE NITRATE 2 g/100 mL; CHLORHEXIDINE GLUCONATE 2 g/100 mL
INACTIVE INGREDIENTS: WATER; SODIUM LAURETH-3 SULFATE; SODIUM LAURYL SULFATE; PROPYLENE GLYCOL; COCAMIDOPROPYL BETAINE; COCO MONOETHANOLAMIDE; GLYCOL STEARATE; PEG-150 DISTEARATE; ALOE VERA LEAF; CITRIC ACID MONOHYDRATE; METHYLCHLOROISOTHIAZOLINONE; METHYLISOTHIAZOLINONE

VetWELL® Micoseb® Topical Shampoo

Active Ingredients:

2% Miconazole Nitrate; 2% Chlorhexidine Gluconate

INDICATIONS AND USAGE

Micoseb Shampoo is a cleansing shampoo that can help improve the condition of skin and coat. Fragrance free and pH-balanced Micoseb Shampoo leaving a coat that is refreshed and clean. It is safe for use on dogs, puppies, cats, kittens, and horses. Good health begins with VetWELL.

Inactive Ingredients:

Purified Water, Sodium Laureth Sulfate, Sodium Lauryl Sulfate, Propylene Glycol, Cocamidopropyl Betaine and Cocamide MEA, Glycol Stearate, PEG 150 Distearate, Aloe Vera, Citric Acid, Methylchloroisothiazolinone (and) Methylisothiazolinone

Directions for Use:

Shake well before using. Wet coat thoroughly with warm water. Apply shampoo to head and ears, then lather. Do not get shampoo into eyes. Repeat procedure with neck, chest middle and hindquarters, finishing with legs. Allow shampoo to be absorbed for 5 to 10 minutes then rinse thoroughly.

Cautions:

For animal use only. Avoid contact with eyes or mucous membranes. Not for Otic use. If undue skin irritation develops or increases, discontinue use and consult a veterinarian. For External Use Only. Keep Out of Reach of Children and Pets.

Formulated for Dogs, Cats, & Horses

Manufactured for:
VetWELL®
Odessa, FL 33556
www.vetwell.com

MFG IN USA